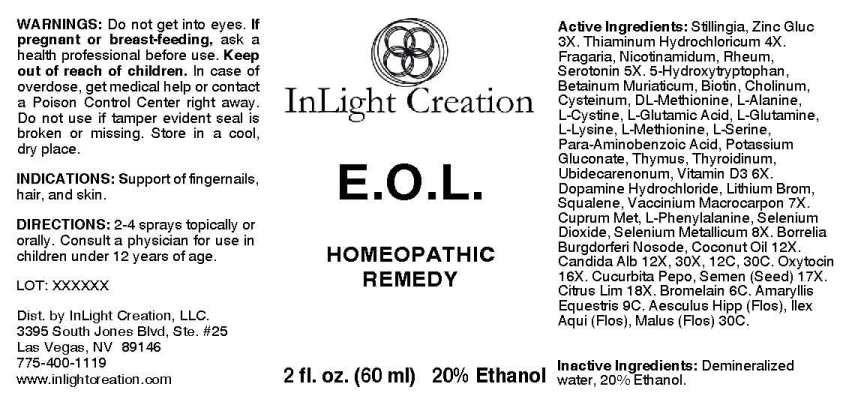 DRUG LABEL: E.O.L.
NDC: 53405-0008 | Form: SPRAY
Manufacturer: InLight Creation, LLC.
Category: homeopathic | Type: HUMAN OTC DRUG LABEL
Date: 20211206

ACTIVE INGREDIENTS: STILLINGIA SYLVATICA ROOT 3 [hp_X]/1 mL; ZINC GLUCONATE 3 [hp_X]/1 mL; THIAMINE HYDROCHLORIDE 4 [hp_X]/1 mL; FRAGARIA VESCA FRUIT 5 [hp_X]/1 mL; NIACINAMIDE 5 [hp_X]/1 mL; RHEUM PALMATUM ROOT 5 [hp_X]/1 mL; SEROTONIN HYDROCHLORIDE 5 [hp_X]/1 mL; OXITRIPTAN 6 [hp_X]/1 mL; BETAINE HYDROCHLORIDE 6 [hp_X]/1 mL; BIOTIN 6 [hp_X]/1 mL; CHOLINE HYDROXIDE 6 [hp_X]/1 mL; CYSTEINE 6 [hp_X]/1 mL; RACEMETHIONINE 6 [hp_X]/1 mL; ALANINE 6 [hp_X]/1 mL; CYSTINE 6 [hp_X]/1 mL; GLUTAMIC ACID 6 [hp_X]/1 mL; GLUTAMINE 6 [hp_X]/1 mL; LYSINE 6 [hp_X]/1 mL; METHIONINE 6 [hp_X]/1 mL; SERINE 6 [hp_X]/1 mL; AMINOBENZOIC ACID 6 [hp_X]/1 mL; POTASSIUM GLUCONATE 6 [hp_X]/1 mL; SUS SCROFA THYMUS 6 [hp_X]/1 mL; SUS SCROFA THYROID 6 [hp_X]/1 mL; UBIDECARENONE 6 [hp_X]/1 mL; CHOLECALCIFEROL 6 [hp_X]/1 mL; DOPAMINE HYDROCHLORIDE 7 [hp_X]/1 mL; LITHIUM BROMIDE 7 [hp_X]/1 mL; SQUALENE 7 [hp_X]/1 mL; CRANBERRY 7 [hp_X]/1 mL; COPPER 8 [hp_X]/1 mL; PHENYLALANINE 8 [hp_X]/1 mL; SELENIUM DIOXIDE 8 [hp_X]/1 mL; SELENIUM 8 [hp_X]/1 mL; BORRELIA BURGDORFERI 12 [hp_X]/1 mL; COCONUT OIL 12 [hp_X]/1 mL; CANDIDA ALBICANS 12 [hp_X]/1 mL; OXYTOCIN 16 [hp_X]/1 mL; PUMPKIN SEED 17 [hp_X]/1 mL; LEMON JUICE 18 [hp_X]/1 mL; BROMELAINS 6 [hp_C]/1 mL; HIPPEASTRUM PUNICEUM WHOLE 9 [hp_C]/1 mL; AESCULUS HIPPOCASTANUM FLOWER 30 [hp_C]/1 mL; ILEX AQUIFOLIUM FLOWERING TOP 30 [hp_C]/1 mL; MALUS DOMESTICA FLOWER 30 [hp_C]/1 mL
INACTIVE INGREDIENTS: WATER; ALCOHOL

DRUG FACTS:

ACTIVE INGREDIENTS:

Stillingia Sylvatica 3X, Zincum Gluconicum 3X, Thiaminum Hydrochloricum 4X, Fragaria Vesca 5X, Nicotinamidum 5X, Rheum (Palmatum) 5X, Serotonin (Hydrochloride) 5X, 5-Hydroxytryptophan 6X, Betainum Muriaticum 6X, Biotin 6X, Cholinum 6X, Cysteinum 6X, DL-Methionine 6X, L-Alanine 6X, L-Cystine 6X, L-Glutamic Acid 6X, L-Glutamine 6X, L-Lysine 6X, L-Methionine 6X, L-Serine 6X, Para-Aminobenzoic Acid 6X, Potassium Gluconate 6X, Thymus (Suis) 6X, Thyroidinum (Suis) 6X, Ubidecarenonum 6X, Vitamin D3 6X, Dopamine Hydrochloride 7X, Lithium Bromatum 7X, Squalene 7X, Vaccinum Macrocarpon 7X, Cuprum Metallicum 8X, L-Phenylalanine 8X, Selenium Dioxide 8X, Selenium Metallicum 8X, Borrelia Burgdorferi Nosode 12X, Coconut Oil 12X, Candida Albicans 12X, 30X, 12C, 30C, Oxytocin 16X, Cucurbita Pepo, Semen 17X, Citrus Limonum 18X, Bromelain 6C, Amaryllis Equestris 9C, Aesculus Hippocastanum, Flos 30C, Ilex Aquifolium, Flos 30C, Malus Pumila, Flos 30C.

INDICATIONS:

Support of fingernails, hair and skin.

WARNINGS:

Do not get into eyes.

If pregnant or breast-feeding, ask a health care professional before use.

Keep out of reach of children. In case of overdose, get medical help or contact a Poison Control Center right away.

Do not use if tamper evident seal is broken or missing.

Store in cool, dry place.

Keep out of reach of children. In case of overdose, get medical help or contact a Poison Control Center right away.

DIRECTIONS:

2-4 sprays topically or orally. Contact a physician for use in children under 12 years of age.

INDICATIONS:

Support of fingernails, hair and skin.

INACTIVE INGREDIENTS:

Demineralized water, 20% Ethanol.

QUESTIONS:

Dist. by InLight Creation, LLC.

3395 South Jones Blvd, Ste. #25

Las Vegas, NV 89146

775-400-1119

www.inlightcreation.com

PACKAGE LABEL DISPALY:

InLight Creation

E.O.L.

HOMEOPATHIC

REMEDY

2 fl. oz. (60 ml)